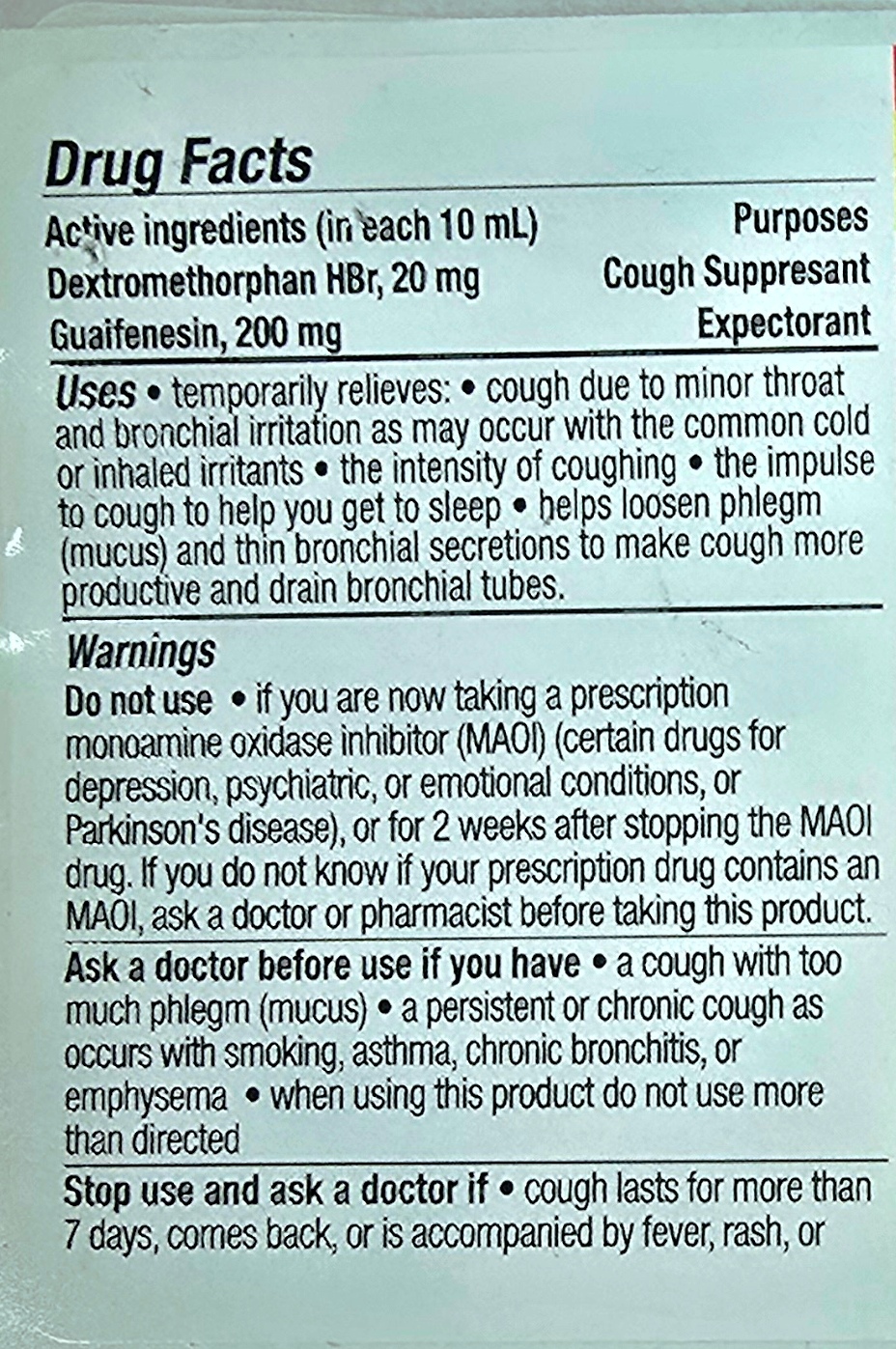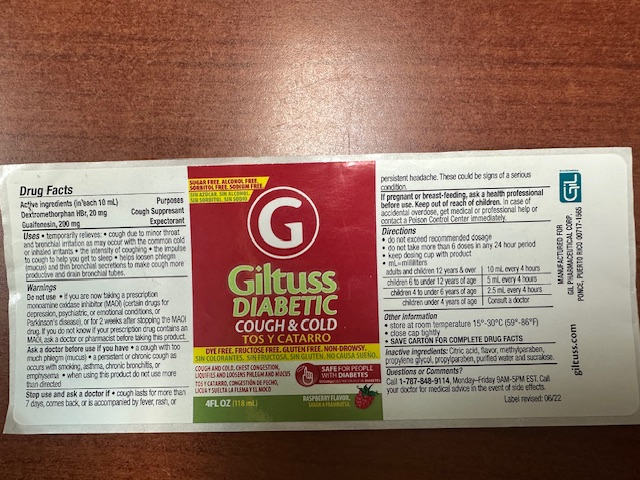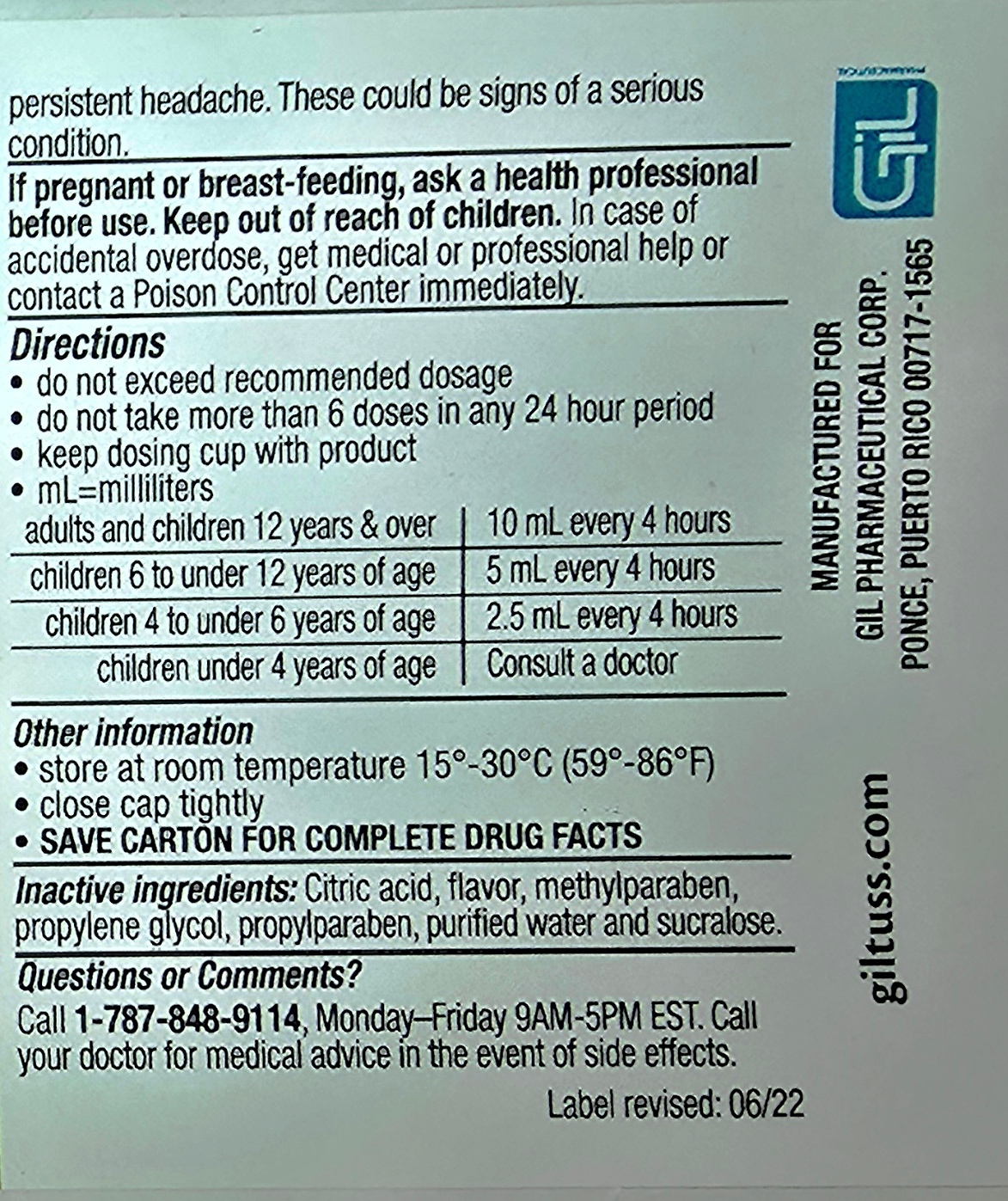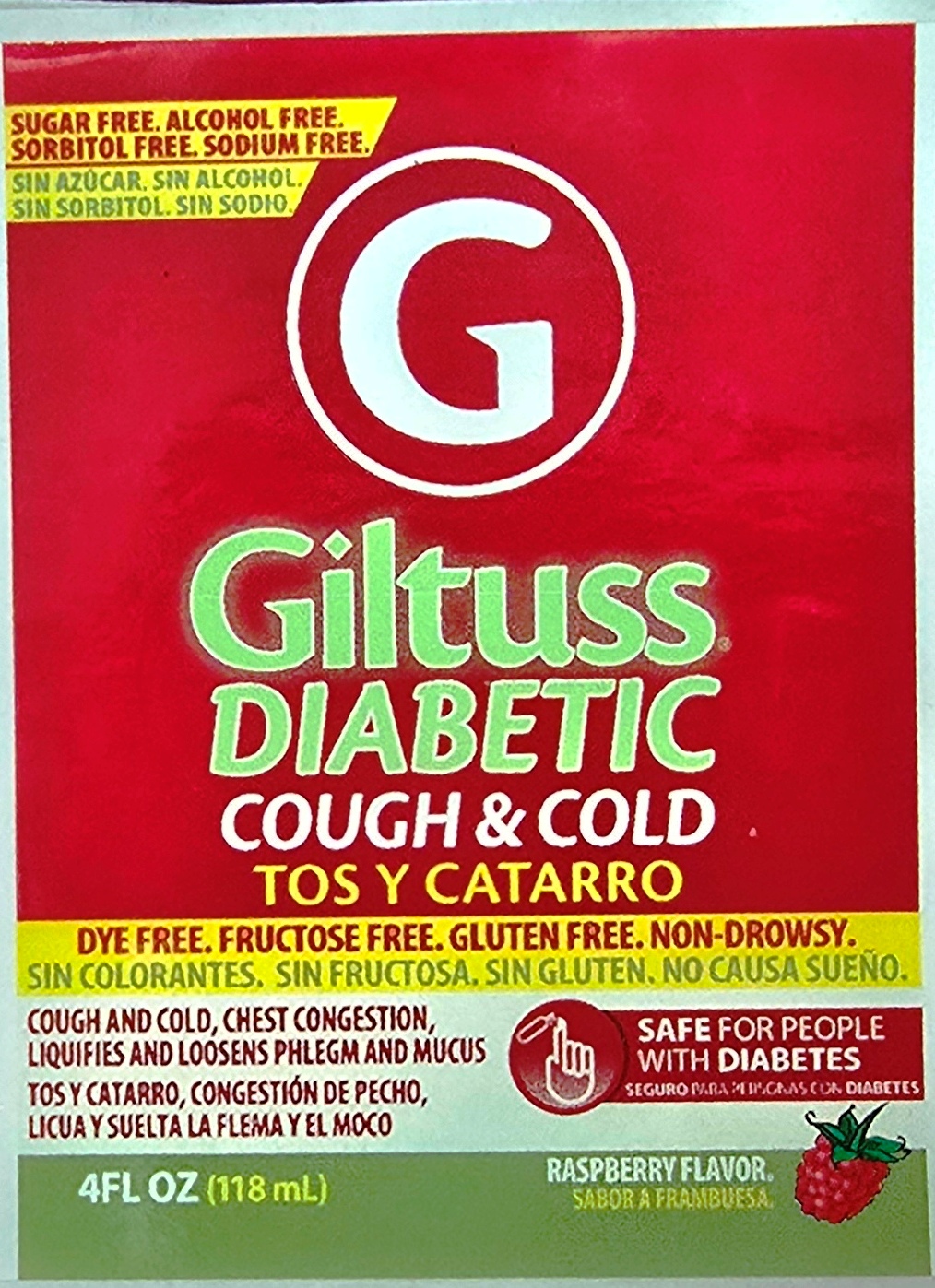 DRUG LABEL: Giltuss Diabetic
NDC: 65852-009 | Form: SOLUTION
Manufacturer: Dextrum Laboratories, Inc
Category: otc | Type: HUMAN OTC DRUG LABEL
Date: 20251006

ACTIVE INGREDIENTS: DEXTROMETHORPHAN HYDROCHLORIDE 20 mg/10 mL; GUAIFENESIN 200 mg/10 mL
INACTIVE INGREDIENTS: METHYLPARABEN; PROPYLPARABEN; WATER; CITRIC ACID; PROPYLENE GLYCOL; SUCRALOSE

Giltuss Diabetic Cough & Cold

Active Ingredients

Dextromethorpan HBr, 20 mg

Guafenesin , 200 mg

Purpose & Uses Section

Purposes

Cough suppresant

Expectorant

Uses

temporary relieves, cough due to minor throat and bronchial irritation as may occur with the common cold or inhaled irritants, the intensity of coughing, the impulse to cough to help you get to sleep, helps loosen phlegm (mucus) and thin bronchial secretions to make cough more productive and drain bronchial tubes.

Warnings

Do not use

If you are taking a prescription monoamine oxidase inhibitor (MAOI) (certains drugs for depression, psychiatric, or emotional conditions, or Parkinson's disease), or for 2 weeks after stopping the MAOI drug. If you dont know is your prescription drug contains and MAOI, ask a doctor or pharmacist before taking this product.

Ask a doctor before use if you have, a cough with too much phlegm(mucus) , a persistent or chronic cough as occurs with smoking, asthma, chronic bronchitis, or emphysema, when using this product do not use more than directed.

Stop use and ask a doctor if

cough lasts for more than 7 days , come back, or is accompanied by fever, rash or persistent headache. These could be signs of serious condition.

If pregnant or breast- feeding, ask a health professional before use. Keep out of reach of childen. In case of accidental overdose, get medical or professional help or contact a Poisson Control center immediatly

Directions

Do not exceed recommended dosage

Do not take more than 6 doses in any 24 hours period

Keep dosing cup with product

ml= mililiters

Adults and children 12 years & over 10 ml every 4 hours

children 6 to under 12 years of age 5 ml every 4 hours

children 4 to under 6 years of age 2.5 ml every 4 hours

children under 4 years of age Consult a doctor

Other information

- Store at room temperature 15-30 °C (59° -86 ° F)
- Close cap tightly
- SAVE CARTON FOR COMPLETE DRUG FACTS

Inactive Ingredients

I

Questions or comments?

Call 1-787-848-9114, Monday-Friday 9AM-5PM EST, Call your doctor for medical advice in the event of side effects.

Label revised :06/22

Indication and usage section

Do nor exceed recommended dosage

Do not take more than 6 doses in any 24 hours period

Adults and children 12 years and over 10 ml every 4 hours

Children 6 to under 12 years age 5 ml every 4 hours

Children 4 to under 6 years age 2.5 ml every 4 hours

Children under 4 years of age Consult a doctor

Keep out of reach of childen.

In case of accidental overdose, get medical or professional help or contact a Poisson Control center immediatly

PACKAGE LABEL

Giltuss Diabetic

Cough & Cold

Sugar Free, Alcohol free, Sorbitol free, Sodium free

Dye free, Fructose free, Gluten free, Non -Drowsy

Cough & Cold, Chest congestion, liquifies and loosens Phlegm and mucus

Safe for people with diabetes

4 floz 118 ml

Rasperry flavor